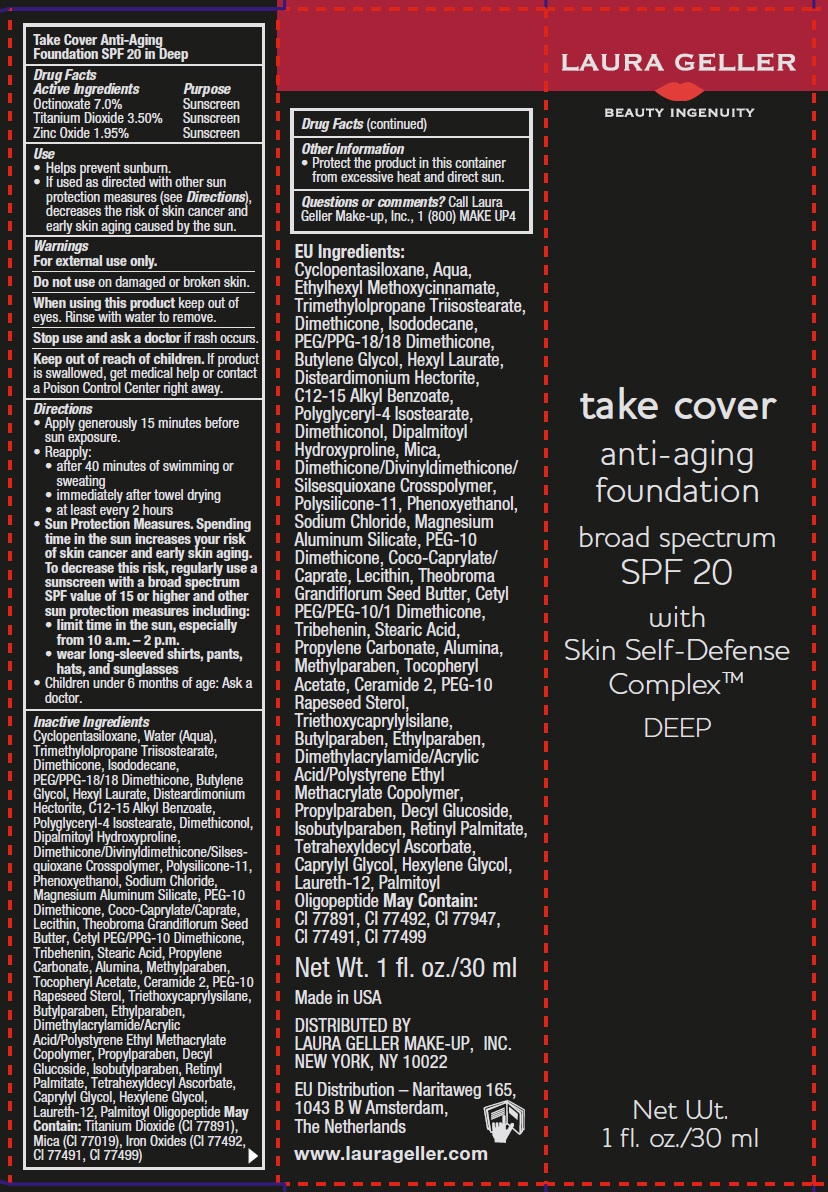 DRUG LABEL: take cover anti-aging foundation
NDC: 51389-118 | Form: CREAM
Manufacturer: LAURA GELLER MAKE UP INC.
Category: otc | Type: HUMAN OTC DRUG LABEL
Date: 20120614

ACTIVE INGREDIENTS: OCTINOXATE 7 g/100 g; TITANIUM DIOXIDE 3.5 g/100 g; ZINC OXIDE 1.95 g/100 g
INACTIVE INGREDIENTS: CYCLOMETHICONE 5; WATER; TRIMETHYLOLPROPANE; DIMETHICONE; ISODODECANE; BUTYLENE GLYCOL; HEXYL LAURATE; ALKYL (C12-15) BENZOATE; POLYGLYCERYL-4 ISOSTEARATE; DIMETHICONOL (250000 MW); DIPALMITOYL HYDROXYPROLINE; PHENOXYETHANOL; SODIUM CHLORIDE; MAGNESIUM ALUMINUM SILICATE; PEG-10 DIMETHICONE (600 CST); THEOBROMA GRANDIFLORUM SEED BUTTER; CETYL PEG/PPG-10/1 DIMETHICONE (HLB 1.5); TRIBEHENIN; STEARIC ACID; PROPYLENE CARBONATE; ALUMINUM OXIDE; METHYLPARABEN; .ALPHA.-TOCOPHEROL ACETATE; CERAMIDE 2; PEG-10 RAPESEED STEROL; TRIETHOXYCAPRYLYLSILANE; BUTYLPARABEN; ETHYLPARABEN; PROPYLPARABEN; DECYL GLUCOSIDE; ISOBUTYLPARABEN; VITAMIN A PALMITATE; TETRAHEXYLDECYL ASCORBATE; CAPRYLYL GLYCOL; HEXYLENE GLYCOL; LAURETH-12; PALMITOYL OLIGOPEPTIDE; FERRIC OXIDE RED; MICA; EGG PHOSPHOLIPIDS; PEG/PPG-18/18 DIMETHICONE

Drug Facts

Active Ingredients

Octinoxate 7.0%
Titanium Dioxide 3.50%
Zinc Oxide 1.95%

Purpose

Sunscreen

Use

- Helps prevent sunburn.
- If used as directed with other sun protection measures (see Directions), decreases the risk of skin cancer and early skin aging caused by the sun.

Warnings

For external use only.

Do not use on damaged or broken skin.

When using this product

Keep out of eyes. Rinse with water to remove.

Stop use and ask a doctor

if rash occurs.

Keep out of reach of children.If product is swallowed, get medical help or contact a Poison Control Center right away.

Directions

- Apply generously 15 minutes before sun exposure.
- Reapply:
-
  - after 40 minutes of swimming or sweating
  - immediately after towel drying
  - at least every 2 hours
- Sun protection measures. Spending time in the sun increases your risk of skin cancer and early skin aging. To decrease this risk, regularly use a sunscreen with a broad spectrum SPF value of 15 or higher and other sun protection measures including:
-
  - limit time in the sun, especially from 10 a.m.- 2 p.m.
  - wear long-sleeved shirts, pants, hats and sunglasses
- Children under 6 months of age: Ask a doctor.

Other Information

- Protect the product in this container from excessive heat and direct sun.

Inactive Ingredients

Cyclopentasiloxane,Water (Aqua), Trimethylolpropane, Triisostearate, Dimethicone, Isododecane, PEG/PPG-18/ 18 Dimethicone, Butylene Glycol, Hexyl Laurate, Disteardimonium Hectorite, C12-C15 Alkyl Benzoate, Polyglyceryl-4 Isostearate, Dimethiconol, Dipalmitoyl Hydroxyproline, Dimethicone/Divinyldimethicone/Silses-quioxane Crosspolymer, Polysilicone-11, Phenoxyethanol, Sodium Chloride, Magnesium Aluminium Silicate, PEG-10 Dimethicone, Coco-Caprylate/Caprate, Lecithin, Theobroma Grandiflorum Seed Butter, Cetyl PEG/PPG-10 Dimethicone, Tribehenin, Stearic Acid, Propylene Carbonate, Alumina, Methylparaben, Tocopheryl Acetate, Ceramide 2, PEG-10 Rapeseed Sterol, Triethoxycaprylysilane, Butylparaben, Ethylparaben, Dimethylacrylamide/Acrylic Acid/Polystyrene Ethyl Methacrylate Copolymer, Propylparaben, Decyl Glucoside, Isobutylparaben, Retinyl Palmitate, Tetrahexyldecyl Ascorbate, Caprylyl Glycol, Hexylene Glycol,Laureth-12, Plamitoyl Oligopeptide May Contain:Titanium Dioxide(CI 77891),Mica(CI 77019), Iron Oxides(CI 77492,CI 77491, CI 77499)

Questions or comments?

Call Laura Geller Make-up, Inc., 1(800) MAKE UP4

Principal Display Panel

LAURA GELLER
BEAUTY INGENUITY
take cover
anti-aging
foundation
broad spectrum
SPF 20
with
Skin Self-Defense
ComplexTM
DEEP
Net Wt.
1 fl. oz./30 ml